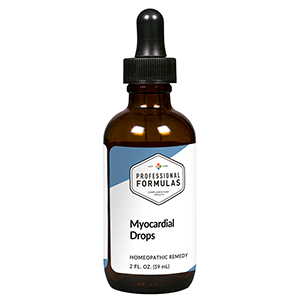 DRUG LABEL: Myocardial Drops
NDC: 63083-5016 | Form: LIQUID
Manufacturer: Professional Complementary Health Formulas
Category: homeopathic | Type: HUMAN OTC DRUG LABEL
Date: 20190815

ACTIVE INGREDIENTS: SELENICEREUS GRANDIFLORUS STEM 3 [hp_X]/59 mL; TERMINALIA ARJUNA WHOLE 3 [hp_X]/59 mL; VALERIAN 3 [hp_X]/59 mL; CONVALLARIA MAJALIS 4 [hp_X]/59 mL; VERATRUM ALBUM ROOT 4 [hp_X]/59 mL; SODIUM TETRACHLOROAURATE 5 [hp_X]/59 mL; SPIGELIA MARILANDICA ROOT 5 [hp_X]/59 mL; GARLIC 6 [hp_X]/59 mL; HAWTHORN LEAF WITH FLOWER 6 [hp_X]/59 mL; DIGITALIS 6 [hp_X]/59 mL; BEEF HEART 6 [hp_X]/59 mL
INACTIVE INGREDIENTS: ALCOHOL; WATER

HMD

ACTIVE INGREDIENTS

Cactus grandiflorus 3X
Terminalia arjuna 3X
Valeriana officinalis 3X
Convallaria majalis 4X
Veratrum album 4X
Aurum muriaticum natronatum 5X
Spigelia marilandica 5X
Allium sativum 6X
Crataegus oxyacantha 6X
Digitalis purpurea 6X
Heart 6X

QUESTIONS

Professional Formulas

PO Box 2034 Lake Oswego, OR 97035

INDICATIONS

For the temporary relief of mild abdominal or chest pain, muscle cramps or spasms, exhaustion, general weakness, dizziness, or anxiousness.*

PURPOSE

*Claims based on traditional homeopathic practice, not accepted medical evidence. Not FDA evaluated.

WARNINGS

Seek medical attention immediately for severe symptoms such as chest pressure or tightness with radiation of the pain to the jaw and down the arm, shortness of breath, or sweating. Keep out of the reach of children. In case of overdose, get medical help or contact a poison control center right away. If pregnant or breastfeeding, ask a healthcare professional before use.

Keep out of the reach of children.

PREGNANCY OR BREAST FEEDING

If pregnant or breastfeeding, ask a healthcare professional before use.

DIRECTIONS

Place drops under tongue 30 minutes before/after meals. Adults and children 12 years and over: Take 10 drops up to 3 times per day. Consult a physician for use in children under 12 years of age.

OTHER INFORMATION

Tamper resistant. If seal is broken, do not use. After opening, close container tightly and store at room temperature away from heat.

INACTIVE INGREDIENTS

20% ethanol, purified water.

LABEL

Est 1985

Professional Formulas

Complementary Health

Myocardial Drops

Homeopathic Remedy

2 FL. OZ. (59 mL)